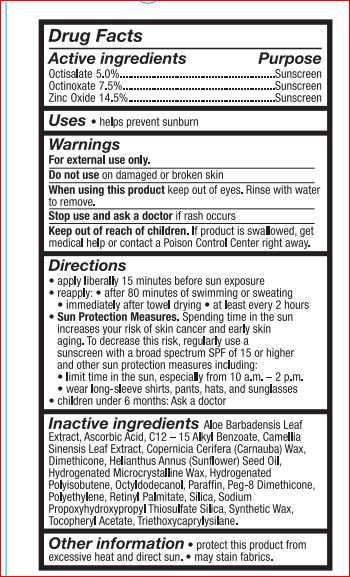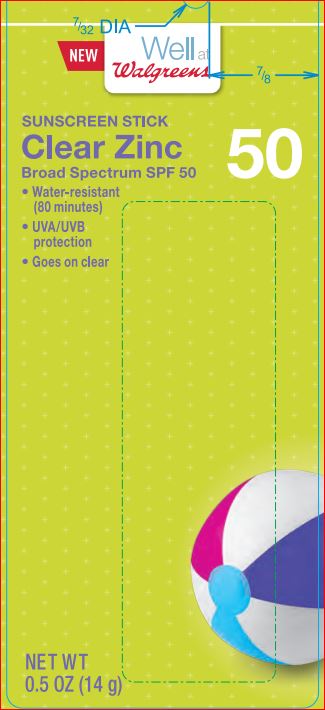 DRUG LABEL: Creal Zink Sunscreen SPF 50
NDC: 0363-1117 | Form: STICK
Manufacturer: Walgreens
Category: otc | Type: HUMAN OTC DRUG LABEL
Date: 20180220

ACTIVE INGREDIENTS: Octinoxate 7.5 g/100 g; Octisalate 5 g/100 g; Zinc Oxide 14.5 g/100 g
INACTIVE INGREDIENTS: ALOE VERA LEAF; ALKYL (C12-15) BENZOATE; GREEN TEA LEAF; CARNAUBA WAX; Dimethicone; SUNFLOWER OIL; Octyldodecanol; PARAFFIN; PEG-8 Dimethicone; HIGH DENSITY POLYETHYLENE; VITAMIN A PALMITATE; SILICON DIOXIDE; SODIUM PROPOXYHYDROXYPROPYL THIOSULFATE SILICA; .ALPHA.-TOCOPHEROL ACETATE; Triethoxycaprylylsilane; ASCORBIC ACID

Drug Facts

Active ingredients Purpose
Octinoxate 7.5% Sunscreen
Octisalate 5.0% Sunscreen
Zinc Oxide 14.5% Sunscreen

INDICATIONS AND USAGE

Uses • helps prevent sunburn

Warnings
For external use only
Flammable: Do not use near heat, flame, or while smoking.
Do not use on damaged or broken skin
When using this product • Keep out of eyes. Rinse eyes with water to
remove. • Keep away from face to avoid breathing it • Do not puncture or
incinerate. Contents under pressure. Do not store at temperatures above 120ºF.
Stop use and ask a doctor if rash occurs

Keep out of reach of children. If product is swallowed, get medical help or contact a Poison Control Center right away.

Directions
• spray liberally and spread evenly by hand 15 minutes before sun exposure
• reapply: • after 80 minutes of swimming or sweating
• immediately after towel drying • at least every 2 hours
• hold container 4 to 6 inches from the skin to apply
• do not spray directly into face. Spray on hands then apply to face.
• do not apply in windy conditions • use in a well-ventilated area
• Sun Protection Measures. Spending time in the sun increases your risk
of skin cancer and early skin aging. To decrease this risk, regularly use a
sunscreen with a broad spectrum SPF of 15 or higher and other sun
protection measures including:
• limit time in the sun, especially from 10 a.m. – 2 p.m.
• wear long-sleeve shirts, pants, hats, and sunglasses
• children under 6 months: Ask a doctor

Inactive ingredients

Aloe Barbadensis Leaf Extract
Ascorbic Acid
C12-15 Alkyl Benzoate
Camellia Sinensis Leaf Extract
Copernicia Cerifera (Carnauba) Wax
Dimethicone
Helianthus Annuus (Sunflower) Seed Oil
Hydrogenated Microcrystalline Wax
Hydrogenated Polyisobutene
Octyldodecanol
Paraffin
PEG-8 Dimethicone
Polyethylene
Retinyl Palmitate
Silica
Sodium Propoxyhydroxypropyl Thiosulfate Silica
Synthetic Wax
Tocopheryl Acetate
Triethoxycaprylylsilane